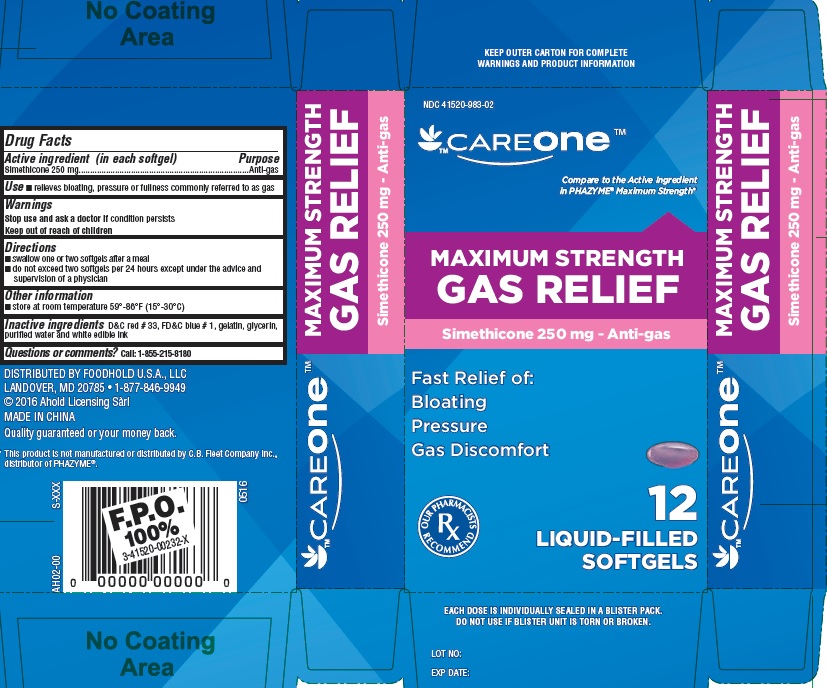 DRUG LABEL: Maximum Strength Gas Relief
NDC: 41520-983 | Form: CAPSULE, LIQUID FILLED
Manufacturer: FOODHOLD U.S.A., LLC
Category: otc | Type: HUMAN OTC DRUG LABEL
Date: 20241121

ACTIVE INGREDIENTS: DIMETHICONE 250 mg/1 1
INACTIVE INGREDIENTS: D&C RED NO. 33; FD&C BLUE NO. 1; GELATIN; GLYCERIN; WATER

MAXIMUM STRENGTH GAS RELIEF

Active ingredient (in each softgel)

Simethicone 250 mg

Purpose

Anti-gas

Use

- relieves bloating, pressure or fullness commonly referred to as gas

Warnings

Stop use and ask a doctor if

condition persists

Keep out of reach of children.

Directions

- swallow one or two softgels after a meal
- do not exceed two softgels per 24 hours except under the advice and supervision of a physician

Other information

- store at room temperature 59°-86°F (15°-30°C)

Inactive ingredients

D&C red #33, FD&C blue #1, gelatin, glycerin, purified water, and white edible ink

Questions or comments?

Call: 1-855-215-8180

PRINCIPAL DISPLAY PANEL

CAREONE MAXIMUM STRENGTH GAS RELIEF

SIMETHICONE 250 mg

Anti-gas

NDC 41520-983-02

Compare to the active ingredient in PHAZYME® Maximum Strength

12 Liquid-Filled SoftGels